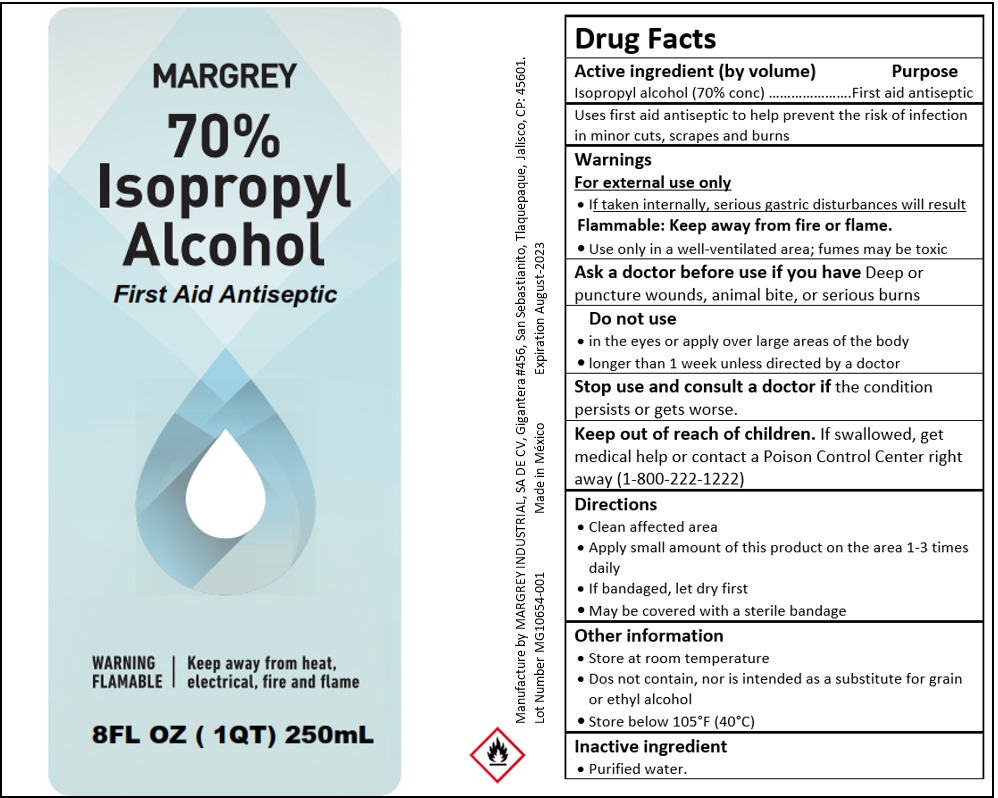 DRUG LABEL: Isopropyl Alcohol
NDC: 77210-0034 | Form: LIQUID
Manufacturer: EXPORTADORA IN AND OUT S DE RL DE CV
Category: otc | Type: HUMAN OTC DRUG LABEL
Date: 20220810

ACTIVE INGREDIENTS: ISOPROPYL ALCOHOL 70 mL/100 mL
INACTIVE INGREDIENTS: WATER 30 mL/100 mL

Purpose

First aid anitseptic
Uses first aid antiseptic to help prevent the risk of infection in minor cuts, scrapes and burns

Acitve ingredient (by volume)
Isopropyl alcohol (70% conc)

For external use only Flammable: keep away from fire or flame

For external use only
-if taken internally, serious gastric disturbances will result
Flammable: keep away from fire and flame
-Use only in a well-ventilated area; fumes may be toxic

Ask a doctor before use if you have

Deep or puncture wounds, animal bite, or serious burns

Do not use

-in eyes or apply over larges areas of the body
-longer than 1 week unless directed by a doctor

Stop use and consult a doctor if

the condition persists or gets worse

Keep out of reach of children

If swallowed, get medical help or contact a Poison Control Center right away (1-800-222-1222)

Directions

-Clean affected area
-Apply small amount of this product on the area 1-3 times daily

-If bandaged, let dry first

-May be covered with a sterile bandage

Directions

-Clean affected area
-Apply small amount of this product on the area 1-3 times daily
-If bandaged, let dry first
-May be covered with a sterile bandage

Other information

-store at room temperature
-does not contain, nor is intended as a subtitute for grain or ethyl alcohol
-store below 105F (40C)

Inactive ingredient

Purified water

Dosage and andministration

Directions
-Clean afected area
-Apply small amount of this product on the area 1-3 times daily
-If bandaged, let dry first
-May be covered with a sterile bandage

Principal Display

MARGREY

70% ISOPROPYL ALCOHOL

First Aid Antiseptic

Warning flammable

Keep away from heat, electrical, fire and flame

8FL (1QT) 250 ml

Manufatured by MARGREY INDUSTRIAL SA DE CV, Gigantera #456, San sebastianito, tlaquepaque, jalisco cp:45601